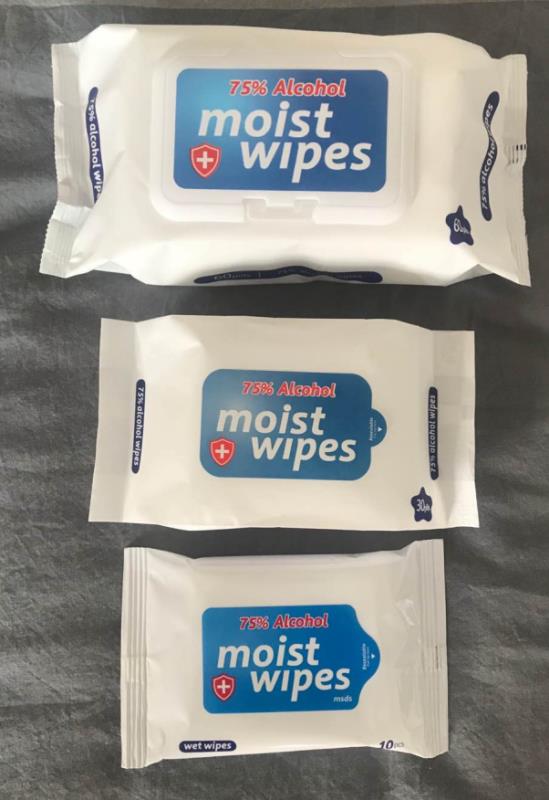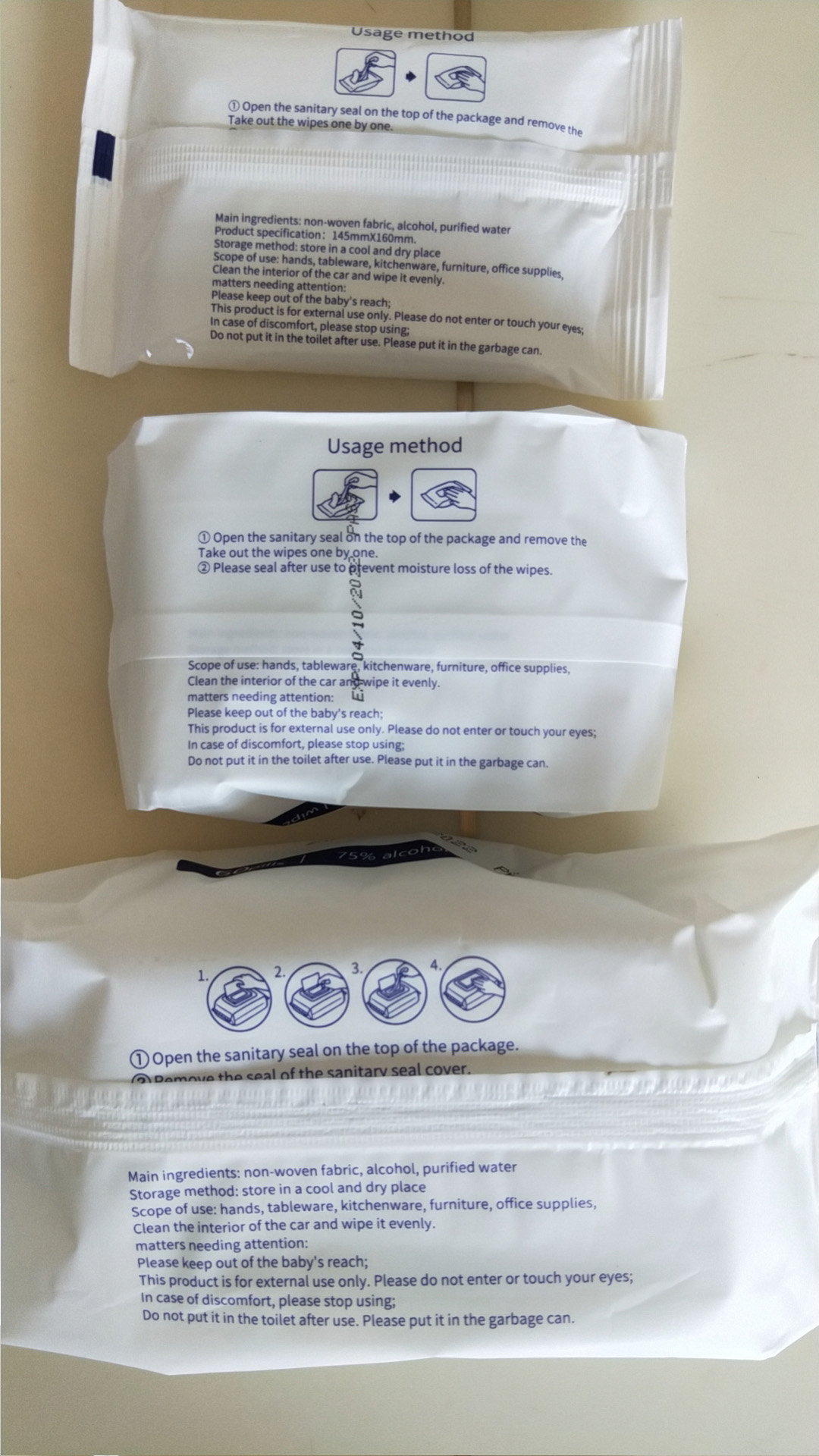 DRUG LABEL: Alcohol moist wipes
NDC: 78451-001 | Form: SWAB
Manufacturer: Liaocheng Yadong Weiye daily necessities Co., Ltd
Category: otc | Type: HUMAN OTC DRUG LABEL
Date: 20200602

ACTIVE INGREDIENTS: ALCOHOL 74.8 g/100 g
INACTIVE INGREDIENTS: WATER

Alcohol moist wipes

ACTIVE INGREDIENT

Ethy| Alcohol 75%

PURPOSE

Antibacterial

USE

Decreases bacteria on skin. Recommended for repeated use

WARNINGS

For external use only.Do not use over large areas of the body if you are allergic to any of the ingredients when using this product,avoid contact with eyes and face.If contact occurs,flush thoroughly with water.Stop use and ask a doctor if irritation or rash develops and continues for more than 72 hours.

Keep out of reach of children. If swallowed, get medical help or contact a Poison Control Center right away.

DIRECTIONS

Foradults and children of 2 years and over.children under 2 years ask a doctor before useallow to dry without wiping.

Directions Peel back flap on front to pull out a towelette.
Unfold and wipe hands thoroughly. Reseal the flap. No need to rinse.

INACTIVE INGREDIENT

Aqua (Water)

PACKAGE LABEL

10 PCS in 1 PACKAGE NDC: 78451-001-01

30 PCS in 1 PACKAGE NDC: 78451-001-02

60 PCS in 1 PACKAGE NDC: 78451-001-03

80 PCS in 1 PACKAGE NDC: 78451-001-04